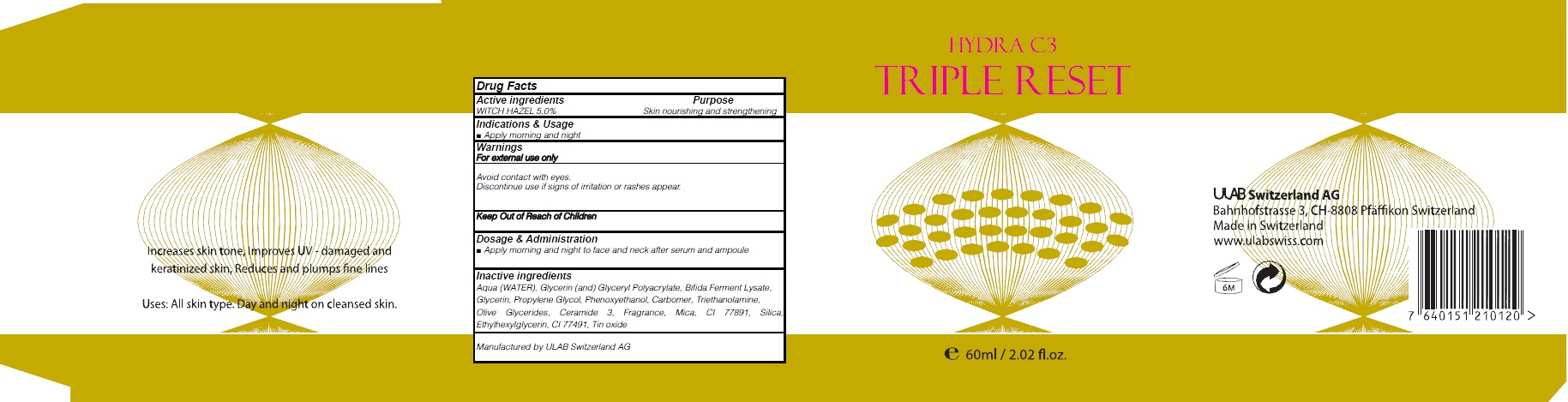 DRUG LABEL: HYDRA C3 TRIPLE RESET
NDC: 71276-100 | Form: CREAM
Manufacturer: ULAB
Category: otc | Type: HUMAN OTC DRUG LABEL
Date: 20170322

ACTIVE INGREDIENTS: WITCH HAZEL 3.0 g/60 mL
INACTIVE INGREDIENTS: WATER; Glycerin

ACTIVE INGREDIENT

Active ingredients: WITCH HAZEL 5.0%

INACTIVE INGREDIENT

Inactive ingredients: Aqua (WATER), Glycerin (and) Glyceryl Polyacrylate, Bifida Ferment Lysate, Glycerin, Propylene Glycol, Phenoxyethanol, Carbomer, Triethanolamine, Olive Glycerides, Ceramide 3, Fragrance, Mica, CI 77891, Silica, Ethylhexylglycerin, CI 77491, Tin oxide

PURPOSE

Purpose: Skin nourishing and strengthening

WARNINGS

Warnings: For external use only Avoid contact with eyes. Discontinue use if signs of irritation or rashes appear.

KEEP OUT OF REACH OF CHILDREN

INDICATIONS & USAGE

Indications & Usage: Apply morning and night

DOSAGE & ADMINISTRATION

Dosage & Administration: Apply morning and night to face and neck after serum and ampoule